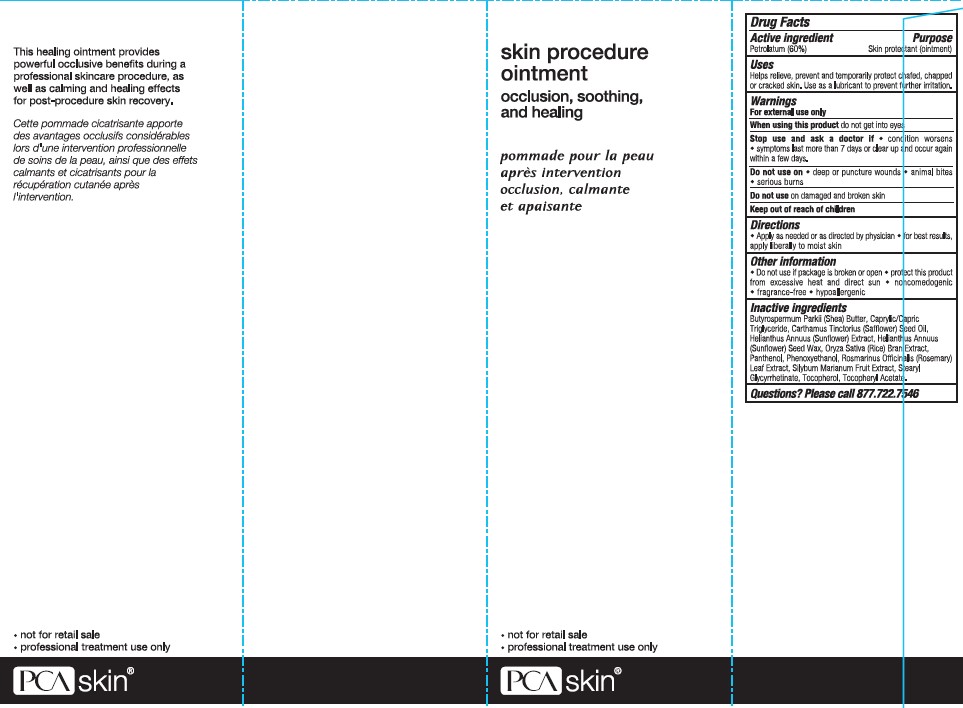 DRUG LABEL: DR527
NDC: 68726-527 | Form: OINTMENT
Manufacturer: Physicians Care Alliance, LLC dba PCA Skin
Category: otc | Type: HUMAN OTC DRUG LABEL
Date: 20211006

ACTIVE INGREDIENTS: PETROLATUM 124 g/207 mL
INACTIVE INGREDIENTS: SAFFLOWER OIL 67 mL/207 mL; PANTHENOL 4 mL/207 mL

Active Ingredient

Petrolatum (60%)

Purpose

Skin protectant (ointment)

Uses

Helps relieve, prevent and temporarily protect chafed, chapped or cracked skin. Use as a lubricant to prevent further irritation.

Warnings

For external use only

When using this product

do not get into eyes

Stop use and ask a doctor it

- condition worsens
- symptoms last more than 7 days or clear up and occur again within a few days

Do not use on

- deep or puncture wounds
- animal bites
- serious burns

Do not use

on damaged and broken skin

Directions

- Apply as needed or as directed by physician
- for best results, apply liberally to moist skin

Other Information

- Do not use if package is broken or open
- protect this product from excessive heat and direct sun
- noncomedogic
- fragrance-free
- hypoallergenic

Questions?

Please call 877.722.7546

Directions

- Apply as needed or as directed by physician
- for best results, apply liberally to moist skin

Inactive Ingredients

Butyrospermum Parkii (Shea) Butter, Caprylic/Capric Triglyceride, Carthamus Tinctorius (Safflower) Seed Oil, Helianthus Annuus (Sunflower) Extract, Helianthus Annuus (Sunflower) Seed Wax, Oryza Sativa (Rice) Bran Extract, Panthenol, Phenoxyethanol, Rosmarinus Officinalis (Rosemary) Leaf Extract, Silybum Marianum Fruit Extract, Stearyl Glycyrrhetinate, Tocopherol, Tocopheryl Acetate.

Uses

- temporarily protects minor: - cuts - scrapes - burns
- helps prevent and temporarily protects and helps relieve chafed, chapped or cracked skin
- helps prevent and protect skin from the drying effects of wind and cold weather